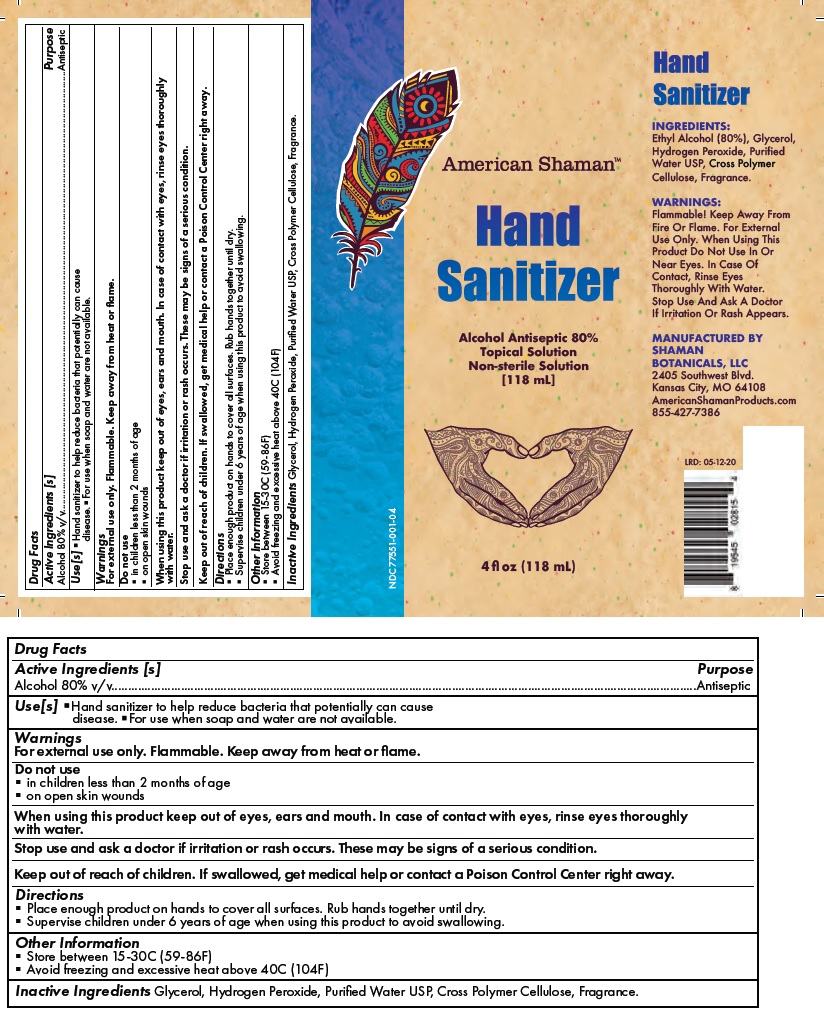 DRUG LABEL: American Shaman Hand Sanitizer
NDC: 77551-001 | Form: LIQUID
Manufacturer: Cbd American Shaman, LLC
Category: otc | Type: HUMAN OTC DRUG LABEL
Date: 20200625

ACTIVE INGREDIENTS: ALCOHOL 80 mL/100 mL
INACTIVE INGREDIENTS: GLYCERIN; HYDROGEN PEROXIDE; WATER; POWDERED CELLULOSE

American ShamanTM Hand Sanitizer

Active Ingredients [s]

Alcohol 80% v/v

Purpose

Antiseptic

Use[s]

•Hand sanitizer to help reduce bacteria that potentially can cause disease. •For use when soap and water are not available.

Warnings

For external use only. Flammable. Keep away from heat or flame.

Do not use

- in children less than 2 months of age
- on open skin wounds

When using this product keep out of eyes, ears and mouth. In case of contact with eyes, rinse eyes thoroughly with water.
Stop use and ask a doctor if irritation or rash occurs. These may be signs of a serious condition.

Keep out of reach of children. If swallowed, get medical help or contact a Poison Control Center right away.

Directions

- Place enough product on hands to cover all surfaces. Rub hands together until dry.
- Supervise children under 6 years of age when using this product to avoid swallowing.

Other Information

- Store between 15-30C (59-86F)
- Avoid freezing and excessive heat above 40C (104F)

Inactive Ingredients

Glycerol, Hydrogen Peroxide, Purified Water USP, Cross Polymer Cellulose, Fragrance.

Alcohol Antiseptic 80%
Topical Solution
Non-sterile Solution

MANUFACTURED BY
SHAMAN BOTANICALS, LLC2405 Southwest Blvd.
Kansas City, MO 64108
AmericanShamanProducts.com
855-427-7386